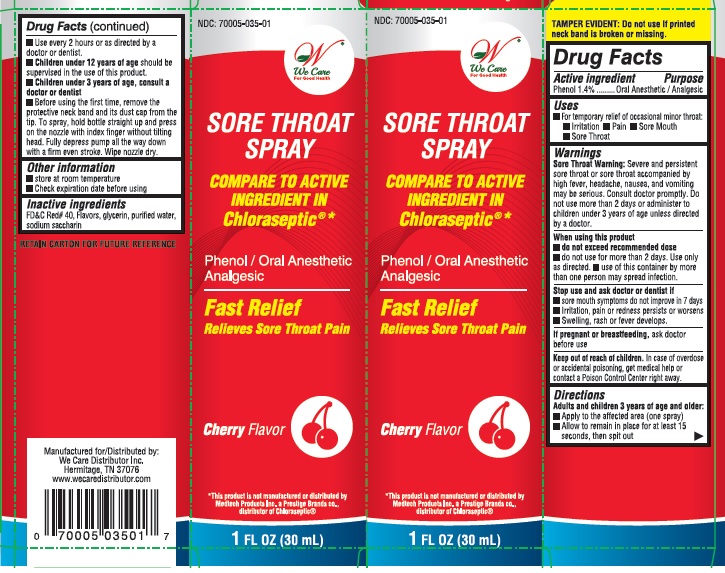 DRUG LABEL: Sore Throat
NDC: 70005-035 | Form: SPRAY
Manufacturer: We Care Distributor Inc.
Category: otc | Type: HUMAN OTC DRUG LABEL
Date: 20160923

ACTIVE INGREDIENTS: PHENOL 1.4 g/100 mL
INACTIVE INGREDIENTS: FD&C RED NO. 40; GLYCERIN; WATER; SACCHARIN SODIUM

Sore Throat

Active ingredient

Phenol 1.4%

Purpose

Oral anesthetic/analgesic

Uses

- For the temporary relief of occasional minor throat:
- irritation
- pain
- sore mouth and
- sore throat

Warnings

Sore throat warning: Severe or persistent sore throat or sore throat accompanied by high fever, headache, nausea, and vomiting may be serious. Consult doctor promptly. Do not use more than 2 days or administer to children under 3 years of age unless directed by a doctor.

When using this product

- do not exceed recommended dose
- do not use for more than 2 days, Use only as directed
- use of this container by more than one person may spread infection

Stop use and ask a doctor or dentist if

- sore mouth symptoms do not improve in 7 days
- irritation, pain or redness persists or worsens
- swelling, rash or fever develops

If pregnant or breast-feeding,

ask doctor before use.

Keep out of reach of children.

In case of overdose or accidental poisoning, get medical help or contact a Poison Control Center right away.

Directions

- Adults and children 3 years of age and older:
- Apply to the affected area (one spray)
- Allow to remain in place for at least 15 seconds, then spit out
- Use every 2 hours or as directed by a doctor or dentist.
- Children under 12 years of age should be supervised in the use of this product
- Children under 3 years of age: consult a doctor or dentist
- Before using the first time, remove the protective neck band and its dust cap from the tip. To spray, hold bottle straight up and press on the nozzle with index finger without tilting head. Fully depress pump all the way down with a firm even stroke. Wipe nozzle dry.

Other information

- store at room temperature
- check expiration date before using
- retain carton for future reference

Inactive ingredients

FD&C red #40, flavor, glycerin, purified water, saccharin sodium

Principal Display Panel

Compare to the Active Ingredient in Chloraseptic

FAST RELIEF

SORE THROAT SPRAY

PHENOL / ORAL ANESTHETIC

CHERRY FLAVOR

Instant-Acting

Relieves Sore Throat

See New Directions